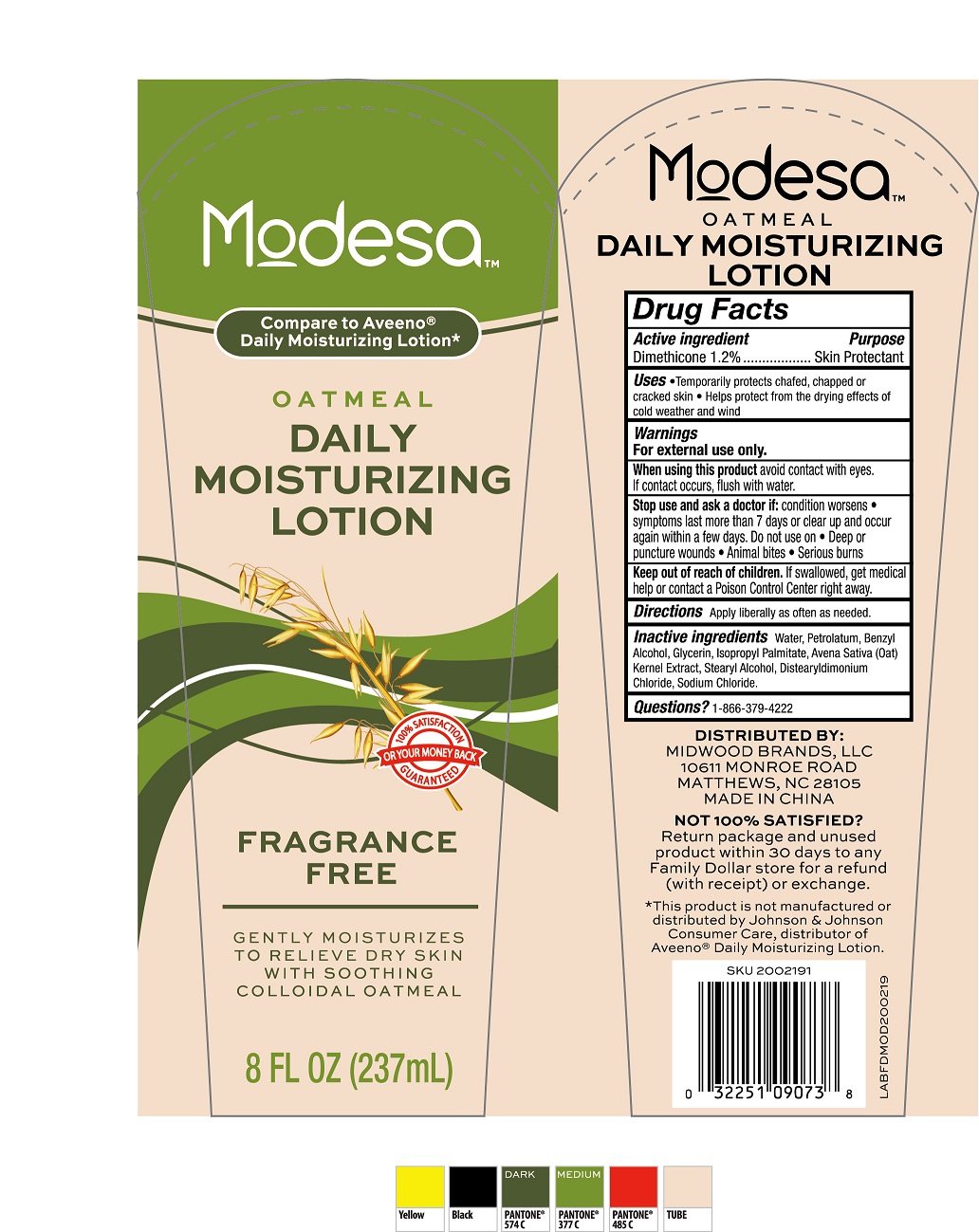 DRUG LABEL: Oatmeal Daily Moisturizing 8oz.
NDC: 58503-107 | Form: LOTION
Manufacturer: China Ningbo Shangge Cosmetic Technology Corp.
Category: otc | Type: HUMAN OTC DRUG LABEL
Date: 20181010

ACTIVE INGREDIENTS: DIMETHICONE 3 g/227 g
INACTIVE INGREDIENTS: WATER; PETROLATUM; GLYCERIN; PROPYLENE GLYCOL; STEARYL ALCOHOL; ISOPROPYL PALMITATE; SODIUM CHLORIDE; OAT KERNEL OIL; BENZYL ALCOHOL; DISTEARYLDIMONIUM CHLORIDE

Oatmeal daily moisturizing lotion (8 oz.)

Active Ingredient Purpose

Dimethicone 1.2% ......... Skin Protectant

PURPOSE

Skin protectant

Keep out of reach of children. If swallowed, get medical help or contact a Poison Control Center immediately.

Uses

- Temporarily protects chafed, chapped or cracked skin
- Helps protect from the drying effects of cold weather and wind

Warnings For external use only.

When using this product avoid contact with eyes. In case of eye contact, flush with water.

Stop use and ask a doctor if condition worsens. Symptoms last more than 7 days or clear up and occur again within a few days.

Do not use on

- Deep or puncture wounds
- Animal bites
- Serious burns

DOSAGE AND ADMINISTRATION

Directions apply liberally as often as needed.

Other Information store at room temperature.

DISTRIBUTED BY:

MIDWOOD BRANDS, INC.

10611 MONROE,

MATTHEWS, NC 28105 USA

MADE IN CHINA

Inactive Ingredients

Water, Petrolatum, Benzyl Alcohol, Glycerin, Isopropyl Palmitate, Avena Sativa (Oat) Kernel Extract, Steraryl Alcohol, Distearyldimonium Chloride, Sodium Chloride